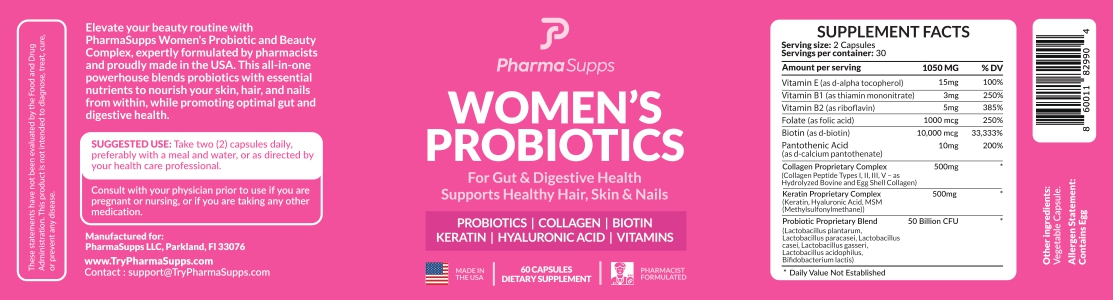 DRUG LABEL: Women Probiotics
NDC: 87260-004 | Form: CAPSULE
Manufacturer: PharmaSupps LLP
Category: other | Type: Dietary Supplement
Date: 20260116

ACTIVE INGREDIENTS: .ALPHA.-TOCOPHEROL 15 mg/1 1; THIAMINE 3 mg/1 1; RIBOFLAVIN 5 mg/1 1; FOLIC ACID 1000 ug/1 1; BIOTIN 10000 ug/1 1; PANTOTHENIC ACID 10 mg/1 1

Women's Probiotics

STATEMENT OF IDENTITY

This statement have not been evaluated by the Food and Drug Administration. This product is not intended to diagnose, treat, cure or prevent any disease.